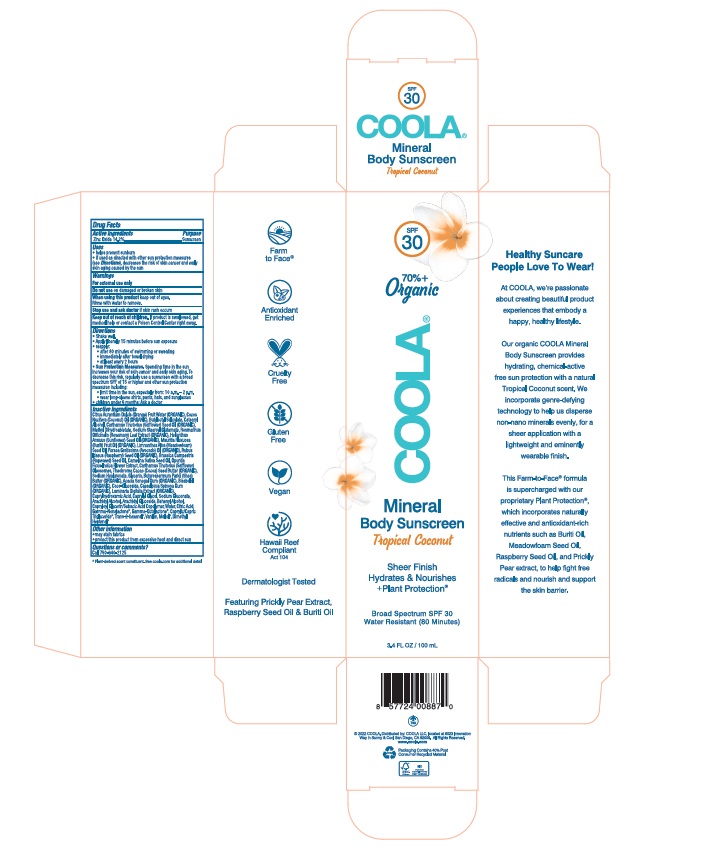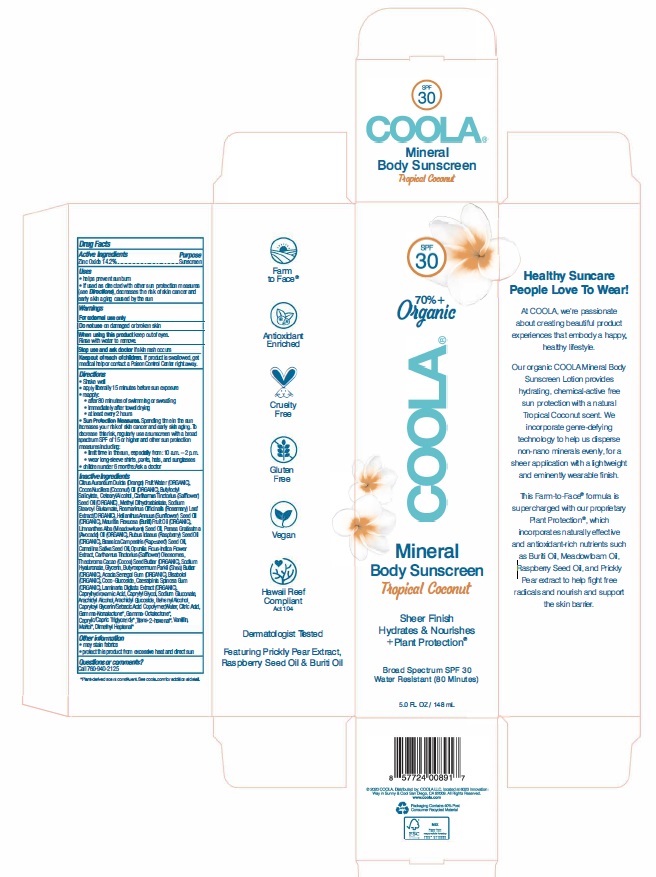 DRUG LABEL: COOLA  Mineral Body SPF 30 Tropical Coconut
NDC: 79753-053 | Form: LOTION
Manufacturer: COOLA, LLC
Category: otc | Type: HUMAN OTC DRUG LABEL
Date: 20241220

ACTIVE INGREDIENTS: ZINC OXIDE 14.2 g/100 mL
INACTIVE INGREDIENTS: CAPRYLYL GLYCOL; ACACIA; SHEA BUTTER; COCOA BUTTER; MEDIUM-CHAIN TRIGLYCERIDES; VANILLIN; OPUNTIA FICUS-INDICA FLOWER; CAPRYLHYDROXAMIC ACID; ARACHIDYL GLUCOSIDE; SODIUM STEAROYL GLUTAMATE; COCO GLUCOSIDE; BUTYLOCTYL SALICYLATE; .GAMMA.-OCTALACTONE; CAMELINA SATIVA SEED OIL; COCONUT OIL; CAESALPINIA SPINOSA RESIN; MEADOWFOAM SEED OIL; .GAMMA.-NONALACTONE; MALTOL; CETOSTEARYL ALCOHOL; LAMINARIA DIGITATA; LEVOMENOL; CAPRYLOYL GLYCERIN/SEBACIC ACID COPOLYMER (2000 MPA.S); SAFFLOWER OIL; MAURITIA FLEXUOSA FRUIT OIL; BRASSICA RAPA SUBSP. OLEIFERA OIL; CARTHAMUS TINCTORIUS (SAFFLOWER) OLEOSOMES; DOCOSANOL; WATER; CITRIC ACID MONOHYDRATE; ORANGE; METHYL DIHYDROABIETATE; HYALURONATE SODIUM; GLYCERIN; RASPBERRY SEED OIL; SODIUM GLUCONATE; ARACHIDYL ALCOHOL; 2-HEXENAL, (2E)-; ROSEMARY; SUNFLOWER OIL; AVOCADO OIL; 2,6-DIMETHYL-5-HEPTENAL

COOLA - Mineral Body Lotion SPF 30 - Tropical Coconut

ACTIVE INGREDIENT

Zinc Oxide - 14.2%

PURPOSE

Sunscreen

Uses

- Helps prevent sunburn
- If used as directed with other sun protection measures (see Directions), decreases the risk of skin cancer and early skin aging caused by the sun

WARNINGS

- For external use only
- Do not use on damaged or broken skin
- When using this product keep out of eyes. Rinse with water to remove.
- Stop use and ask a doctor if skin rash occurs.

Keep out of reach of children. If product is swallowed, get medical help or contact a Poison Control Center right away.

Directions

- Shake well
- Apply liberally 15 minutes before sun exposure
- Reapply: • After 80 minutes of swimming or sweating. • Immediately after towel drying. • At least every 2 hours
- Sun Protection Measure: Spending time in the sun increases your risk of skin cancer and early skin aging. To decrease this risk, regularly use a sunscreen with a broad spectrum SPF value of 15 or higher and other sun protection measures including: • Limit time in the sun, especially from 10 a.m. to 2 p.m. • Wear long-sleeved shirts, pants, hats, and sun glasses.

INACTIVE INGREDIENT

Citrus Aurantium Dulcis (Orange) Fruit Water (ORGANIC), Cocos Nucifera (Coconut) Oil (ORGANIC), Butyloctyl Salicylate, Cetearyl Alcohol, Carthamus Tinctorius (Safflower) Seed Oil (ORGANIC), Methyl Dihydroabietate, Sodium Stearoyl Glutamate, Coco-Glucoside, Acacia Senegal Gum (ORGANIC), Caesalpinia Spinosa Gum (ORGANIC), Sodium Hyaluronate, Glycerin, Laminaria Digitata Extract (ORGANIC), Butyrospermum Parkii (Shea) Butter (ORGANIC), Theobroma Cacao (Cocoa) Seed Butter (ORGANIC), Bisabolol (ORGANIC), Rosmarinus Officinalis (Rosemary) Leaf Extract (ORGANIC), Helianthus Annuus (Sunflower) Seed Oil (ORGANIC), Mauritia Flexuosa Fruit Oil (ORGANIC), Limnanthes Alba (Meadowfoam) Seed Oil, Persea Gratissima (Avocado) Oil (ORGANIC), Rubus Idaeus (Raspberry) Seed Oil (ORGANIC), Brassica Campestris (Rapeseed) Seed Oil, Camelina Sativa Seed Oil, Opuntia Ficus-Indica Flower Extract, Carthamus Tinctorius (Safflower) Oleosomes, Caprylhydroxamic Acid, Caprylyl Glycol, Sodium Gluconate, Arachidyl Alcohol, Arachidyl Glucoside, Behenyl Alcohol, Capryloyl Glycerin/Sebacic Acid Copolymer, Water, Citric Acid, Gamma-Nonalactone, Gamma-Octalactone, Caprylic/Capric Triglyceride, Trans-2-hexenal, Vanillin, Maltol, Dimethyl Heptenal

OTHER SAFETY INFORMATION

- May stain fabrics
- Protect this product from excessive heat and direct sun

QUESTIONS

Call 760-940-2125